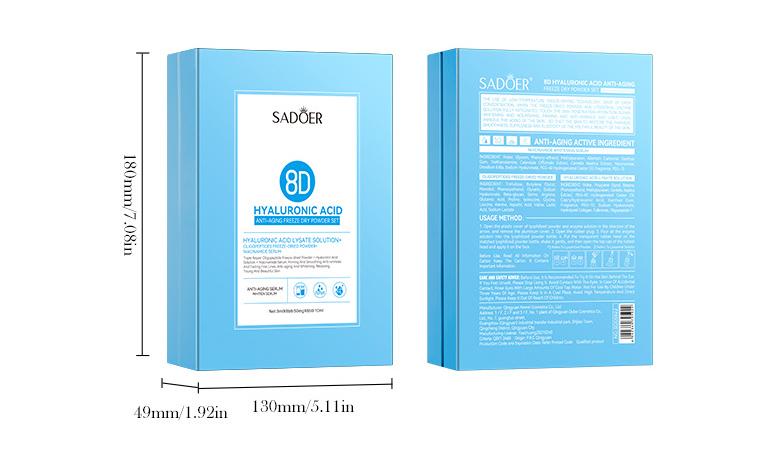 DRUG LABEL: Hyaluronic acid freeze-dried powder
NDC: 84775-063 | Form: EMULSION
Manufacturer: Shenzhen Fusian Technology Co Ltd
Category: otc | Type: HUMAN OTC DRUG LABEL
Date: 20241127

ACTIVE INGREDIENTS: HYALURONIC ACID 10 mg/50 mg; TREHALOSE 10 mg/50 mg; WATER 10 mg/50 mg
INACTIVE INGREDIENTS: GLYCERIN 20 mg/50 mg

ACTIVE INGREDIENT

WATER 40%

GLYCERIN 20%

HYALURONIC ACID 20%

TREHALOSE 20%

PURPOSE

Moisturizing

INDICATIONS USAGE SECTION

Hyaluronic acid freeze-dried powder is a skin care product that mainly replenishes water and repairs, and is widely used to improve a variety of skin problems. The following are its main indications:

1. Dehydrated skin

Symptoms:
The skin is dry, rough, and tight, and even peeling occurs.

Functions:
Hyaluronic acid freeze-dried powder can deeply replenish water, enhance the skin's moisturizing ability, and relieve dryness symptoms.

2. Damaged skin barrier

Symptoms:
Skin is sensitive, red, swollen, and easily inflamed, and even tingling occurs, and the barrier function is weakened.

Functions:
Repair the skin barrier, promote the repair and regeneration of damaged skin, and improve the sensitive state.

3. Early fine lines and dry lines

Symptoms:
Dry lines and superficial fine lines at the corners of the eyes and mouth caused by water loss.

Functions:
Replenish skin moisture, improve fine lines caused by dryness, and make the skin look smoother and more elastic.

4. Dull and dull skin

Symptoms:
The skin is rough, lacks luster, and looks tired.

Functions:
Improve skin moisture, improve dullness, and restore skin translucency.
5. Skin with acne and acne marks
Symptoms:
Pigmentation and acne marks are left after acne heals, or the skin's ability to repair is weak.
Function:
Accelerates acne repair, helps fade acne marks, and promotes skin self-repair.
6. Sensitive skin
Symptoms:
Strong reaction to external stimuli (such as wind, temperature difference), prone to redness and fever.
Function:
Calms and soothes the skin, reduces irritation, and enhances skin tolerance.
7. Early aging skin
Symptoms:
Sagging and dry skin accompanied by loss of collagen, showing signs of aging.
Function:
Replenishes moisture and locks in moisture, while maintaining skin elasticity and delaying skin aging.

WARNINGS

Please keep out of reach of children,Do not swallow,

Please clean your hands before use to ensure the best

resuits fromthe product. Discontinue use if signs of irritation

or rash occur. Store in a cool and dry place.

STOP USE SECTION

iscontinue use if signs of irritation or rash occur

Do not use

on damaged or broken skin

Keep out of reach of children!

lf swallowed, get medical heip or contact a Poison Control Center right away

When using this product

How to use:
Face care:
Mix 1-2 drops of turmeric essential oil with a base oil (such as jojoba oil or sweet almond oil) and apply to the face.
Use every night to avoid photosensitivity caused by UV rays during the day.
Body care:
Add a few drops of turmeric essential oil to lotion or body oil and apply to the whole body to help even out skin tone.
Mask addition:
Mix 1 drop of turmeric essential oil into a natural mud mask or homemade mask, apply for 10-15 minutes and then wash off.
Topical use:
For spots or acne marks, dilute the essential oil and apply it to the target area with a cotton swab.
Bath method:
Add a few drops of turmeric essential oil to warm water to soothe and whiten the skin all over the body.

Directions

How to use:
Cleaning the skin:
Before use, thoroughly clean the skin with a mild cleansing product to ensure that the skin is clean and free of impurities.

Diluting the freeze-dried powder:

The freeze-dried powder is usually mixed with a matching solvent (such as hyaluronic acid stock solution or a specific dissolving solution).
Open the freeze-dried powder and the solvent and mix the two evenly according to the product instructions.
After mixing, you can gently shake the container to ensure complete dissolution.
Apply to the skin:

Apply an appropriate amount of dissolved hyaluronic acid freeze-dried powder liquid evenly on the face or the area that needs care.
Can be combined with gentle massage to promote absorption.
Subsequent skin care:

After using the freeze-dried powder liquid, you can continue to apply cream, lotion or sunscreen products to lock in moisture.
It is recommended to use it at night for better results.
Dosage recommendation:
Daily care: Use about 1-2 ml each time (adjust according to personal needs).
Key repair: The frequency of use can be increased appropriately, usually 1-2 times a day (once in the morning and once in the evening).
Course of use: It is generally recommended to use it continuously for about 4 weeks, and then adjust the frequency of use according to the skin condition.

INACTIVE INGREDIENT SECTION

Niacinamide

Hydrolyzed Collagen